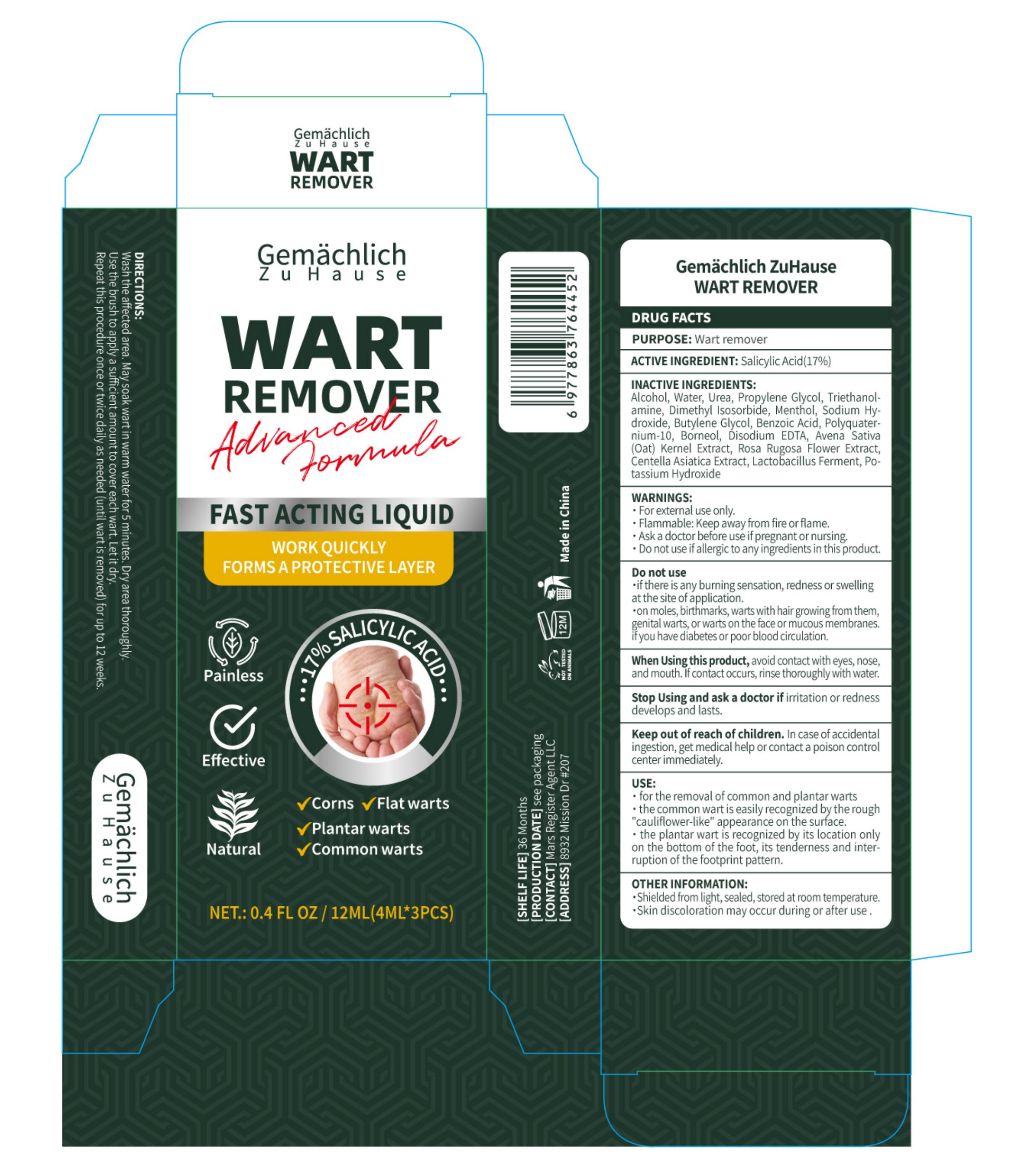 DRUG LABEL: Gemachlich ZuHause WART REMOVER
NDC: 76986-018 | Form: LIQUID
Manufacturer: Guangdong Quadrant Ecological Technology Co., Ltd.
Category: otc | Type: HUMAN OTC DRUG LABEL
Date: 20251215

ACTIVE INGREDIENTS: SALICYLIC ACID 17 g/100 mL
INACTIVE INGREDIENTS: PROPYLENE GLYCOL; BUTYLENE GLYCOL; ALCOHOL; UREA; TRIETHANOLAMINE; DIMETHYL ISOSORBIDE; MENTHOL; CENTELLA ASIATICA TRITERPENOIDS; OAT; ROSA RUGOSA FLOWER; SODIUM HYDROXIDE; BORNEOL; EDETATE DISODIUM; WATER; BENZOIC ACID; POLYQUATERNIUM-10 (125 MPA.S AT 2%); LACTOBACILLUS REUTERI F275 STRAIN; POTASSIUM HYDROXIDE

76986-018

Active Ingredient

Salicylic Acid 17%

Purpose

Wart remover

Use

· for the removal of common and plantar warts
· the common wart is easily recognized by the rough "cauliflower-like"appearance on the surface.
· the plantar wart is recognized by its location only on the bottom of the foot, its tenderness and interruption of the footprint pattern.

Warnings

· For external use only.
· Flammable: Keep away from fire or flame.
· Ask a doctor before use if pregnant or nursing.
· Do not use if allergic to any ingredients in this product.

Do not use

·if there is any burning sensation, redness or swelling at the site of application.
·on moles, birthmarks, warts with hair growing from them, genital warts, or warts on the face or mucous membranes.

·if you have diabetes or poor blood circulation.

When Using

avoid contact with eyes, nose and mouth. If contact occurs, rinse thoroughly with water.

Stop Use

Stop Using and ask a doctor if irritation or redness develops and lasts.

Ask Doctor

Stop Using and ask a doctor if irritation or redness develops and lasts.

Keep Out Of Reach Of Children

In case of accidental ingestion, get medical help or contact a poison control center immediately.

Directions

Wash the affected area.May soak wart in warm water for 5 minutes.Dry area thoroughly.Use the brush to apply a sufficient amount to cover each wart. Let it dry.
Repeat this procedure once or twice daily as needed (until wart is removed) for up to12 weeks.

Other information

·Shielded from light, sealed, stored at room temperature.
·Skin discoloration may occur during or after use .

Inactive ingredients

Alcohol, Water, Urea, Propylene Glycol, Triethanolamine, Dimethyl Isosorbide, Menthol, Sodium Hydroxide, Butylene Glycol, Benzoic Acid, Polyquaternium-10, Borneol, Disodium EDTA, Avena Sativa (Oat) Kernel Extract, Rosa Rugosa Flower Extract, Centella Asiatica Extract, Lactobacillus Ferment, Potassium Hydroxide